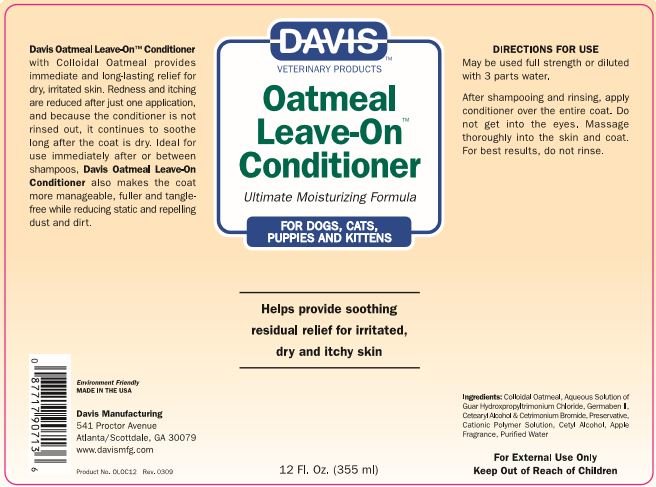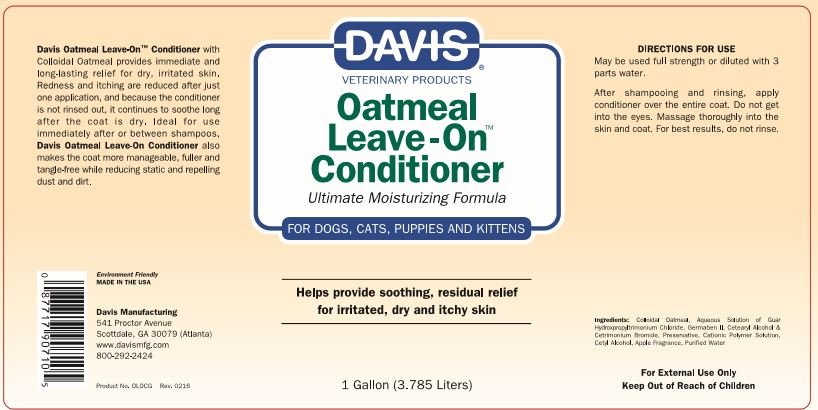 DRUG LABEL: Davis Oatmeal Leave On
NDC: 62570-081 | Form: LOTION
Manufacturer: Davis Manufacturing and Packaging Inc
Category: animal | Type: OTC ANIMAL DRUG LABEL
Date: 20191111

ACTIVE INGREDIENTS: OATMEAL 1 g/100 g
INACTIVE INGREDIENTS: water; CETYL ALCOHOL; CETOSTEARYL ALCOHOL; CETRIMONIUM BROMIDE; POLYQUATERNIUM-47 (METHACRYLAMIDOPROPYLTRIMETHYLAMMONIUM CHLORIDE-CO-METHYL ACRYLATE-CO-ACRYLIC ACID 45:10:45; 1200000 MW); GUAR HYDROXYPROPYLTRIMONIUM CHLORIDE (1.7 SUBSTITUENTS PER SACCHARIDE); DIAZOLIDINYL UREA

Davis Oatmeal Leave-OnTM Conditioner

DESCRIPTION

Davis Leave-OnTM Conditioner with Colloidal Oatmeal provides immediate and long-lasting relief for dry, irritated skin. Redness and itching are reduced after just one application, and because conditioner is not rinsed out, it continues to soothe long after the coat is dry. Ideal for use immediately after or between shampoos, Davis Oatmeal Leave-on Conditioner also makes the coat more manageable, fuller and tangle-free while reducing static and repelling dust and dirt.

Environment Friendly

MADE IN THE USA

Davis Manufacturing

541 Proctor Avenue

Scottdale, GA 30079 (Atlanta)

800-292-2424

DOSAGE AND ADMINISTRATION

May be used full strength or diluted with 3 parts water.

INSTRUCTIONS FOR USE

After shampooing and rinsing, apply conditioner over the entire coat. Do not get into eyes. Massage thoroughly into the skin and coat. For best results do not rinse.

Ingredients

Ingredients: Colloidal Oatmeal, Aqueous Solution of Guar Hydroxpropyltrimonium Chloride, Germaben II, Cetearyl Alcohol & Cetyl Alcohol, Apple Fragrance, Purified Water

WARNINGS AND PRECAUTIONS

FOR EXTERNAL USE ONLY

KEEP OUT OF REACH OF CHILDREN

Principal Display 355 ml

Davis Veterinary Products

Oatmeal Leave-On TM Conditioner

Ultimate Mositurizing Formula

FOR DOGS, CATS, PUPPIES, AND KITTENS

Helps provide soothing residual relief for irritated, dry and itchy skin

12 Fl. Oz (355 ml)

PACKAGE LABEL

Davis Veterinary Products Oatmeal Leave-On TM Conditioner

Ultimate Mositurizing Formula FOR DOGS, CATS, PUPPIES, AND KITTENS

Helps provide soothing residual relief for irritated, dry and itchy skin

1 Gallon (3.785 Liters)